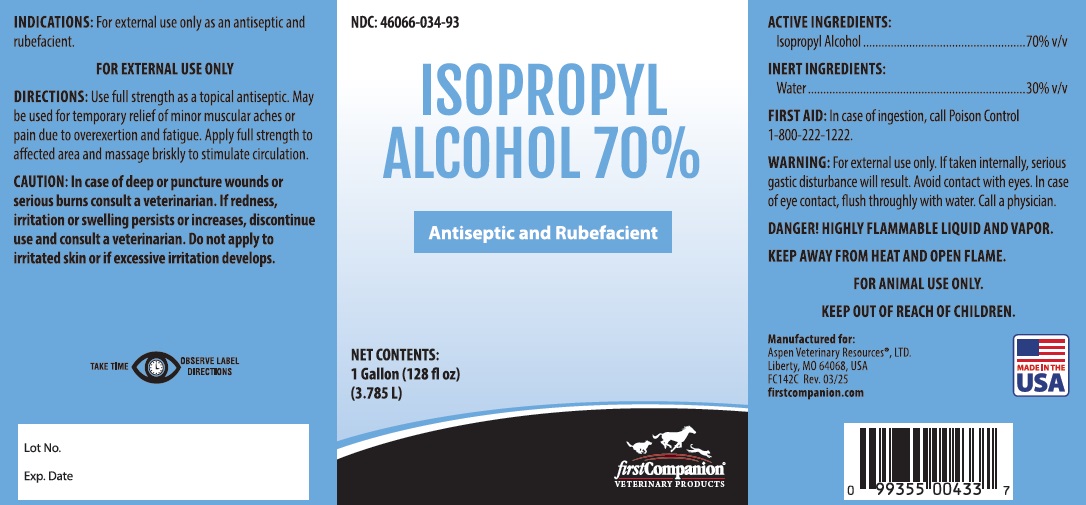 DRUG LABEL: Isopropyl Alcohol 70 percent
NDC: 46066-034 | Form: SOLUTION
Manufacturer: Aspen Veterinary Resources
Category: animal | Type: OTC ANIMAL DRUG LABEL
Date: 20250417

ACTIVE INGREDIENTS: ISOPROPYL ALCOHOL 0.70 g/3785 g
INACTIVE INGREDIENTS: WATER 0.30 g/3785 g

WARNINGS AND PRECAUTIONS

Isopropyl Alcohol 70%

Antiseptic and Rubefacient

ACTIVE INGREDIENTS:

Isopropyl Alcohol ............................ 70%v/v

INERT INGREDIENTS:

Water ........................................... 30%v/v

FIRST AID: In case of ingestion, call Poison Control 1-800-222-1222.

WARNING: For external use only. If taken internally, serious gastric disturbance will result. Avoid contact with eyes. In case of eye contact, flush throughly with water. Call a physician.

DANGER! HIGHLY FLAMMABLE LIQUID AND VAPOR.

KEEP AWAY FROM HEAT AND OPEN FLAME.

FOR ANIMAL USE ONLY.

Keep Out of Reach of Children.

INDICATIONS: For external use only as an antiseptic and rubefacient.

FOR EXTERNAL USE ONLY

DIRECTIONS: Use full strength as topical antiseptic. May be used for temporary relief of minor muscular aches or pain due to overexertion and fatigue. Apply full strength to affected area and massage briskly to stimulate circulation.

CAUTION: In case of deep or puncture wounds or serious burns, consult a veterinarian. If redness, irritation, or swelling persists or increases, discontinue use and consult a veterinarian. Do not apply to irritated skin or if excessive irritation develops.

STORAGE: Store Between 59°-86°F (15°-30°C). Keep container closed with not in use.

Manufactured for:

Aspen Veterinary Resources, Ltd.

Liberty, MO 64068, USA

FC143C

Made in the USA.

Rev. 03/25